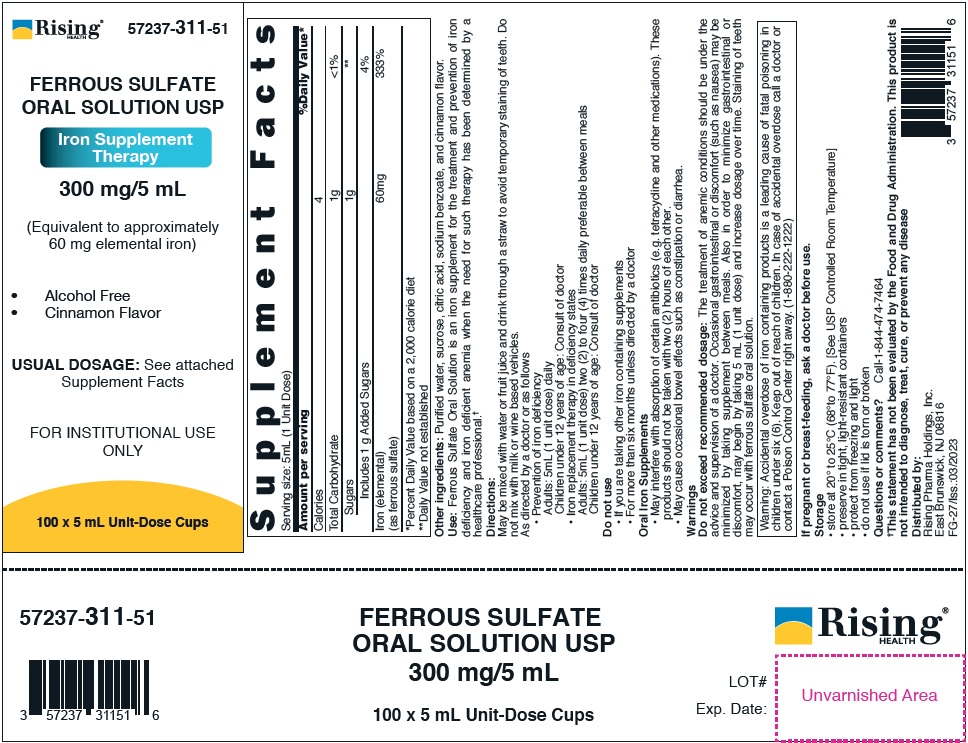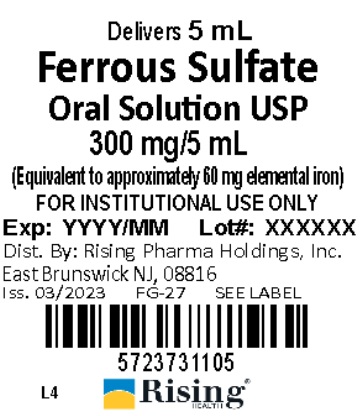 DRUG LABEL: FERROUS SULFATE
NDC: 57237-311 | Form: SOLUTION
Manufacturer: Rising Pharma Holdings, Inc.
Category: other | Type: DIETARY SUPPLEMENT
Date: 20250512

ACTIVE INGREDIENTS: FERROUS SULFATE 300 mg/5 mL
INACTIVE INGREDIENTS: CITRIC ACID MONOHYDRATE; SODIUM BENZOATE; SUCROSE; WATER

Ferrous Sulfate Oral Solution USP
Iron Supplement Therapy
300 mg/5 mL
(Equivalent to approximately 60 mg elemental iron)
• Alcohol Free
• Cinnamon Flavor
FOR INSTITUTIONAL USE ONLY

STATEMENT OF IDENTITY

Supplement Facts
Serving Size: 5mL (1 Unit Dose)
Amount per serving |  | % Daily Value*
Calories | 4
Total Carbohydrate | 1g | <1%
Sugars | 1g | **
Includes 1g Added Sugars |  | 4%
Iron (elemental) (as ferrous sulfate) | 60mg | 333%
*Percent Daily Value based on a 2,000 calorie diet **Daily Value not established

HEALTH CLAIM

Other ingredients: Purified water, sucrose, citric acid, sodium benzoate, and cinnamon flavor.

Use: Ferrous Sulfate Oral Solution is an iron supplement for the treatment and prevention of iron deficiency and iron deficient anemia when the need for such therapy has been determined by a healthcare professional.†

Directions:

May be mixed with water or fruit juice and drink through a straw to avoid temporary staining of teeth. Do not mix with milk or wine based vehicles.
As directed by a doctor or as follows

- Prevention of iron deficiency
  Adults: 5mL (1 unit dose) daily
  Children under 12 years of age: Consult of doctor
- Iron replacement therapy in deficiency states
  Adults: 5mL (1 unit dose) two (2) to four (4) times daily preferable between meals
  Children under 12 years of age: Consult of doctor

Do not use

- If you are taking other iron containing supplements
- For more than six months unless directed by a doctor

Oral Iron Supplements

- May interfere with absorption of certain antibiotics (e.g. tetracycline and other medications). These products should not be taken with two (2) hours of each other.
- May cause occasional bowel effects such as constipation or diarrhea.

Warnings

Do not exceed recommended dosage: The treatment of anemic conditions should be under the advice and supervision of a doctor. Occasional gastrointestinal or discomfort (such as nausea) may be minimized by taking supplement between meals. Also in order to minimize gastrointestinal or discomfort, may begin by taking 5 mL (1 unit dose) and increase dosage over time. Staining of teeth may occur with ferrous sulfate oral solution.

Warning: Accidental overdose of iron containing products is a leading cause of fatal poisoning in children under six (6). Keep out of reach of children. In case of accidental overdose call a doctor or contact a Poison Control Center right away. (1-880-222-1222)

PRECAUTIONS

If pregnant or breast-feeding, ask a doctor before use.

DOSAGE AND ADMINISTRATION

Storage

• store at 20° to 25°C (68°to 77°F). [See USP Controlled Room Temperature]
• preserve in tight, light-resistant containers
• protect from freezing and light
• do not use if lid is torn or broken

Questions or comments? Call-1-844-474-7464
†This statement has not been evaluated by the Food and Drug Administration. This product is not intended to diagnose, treat, cure, or prevent any disease

Distributed by:
Rising Pharma Holdings, Inc.
East Brunswick, NJ 08816
FG-27/Iss.:03/2023

PACKAGE LABEL

Case label -57237-311-51 (100 x 5 mL Unit-Dose Cups)

Lid Label -57237-311-05 (Delivers 5 mL)